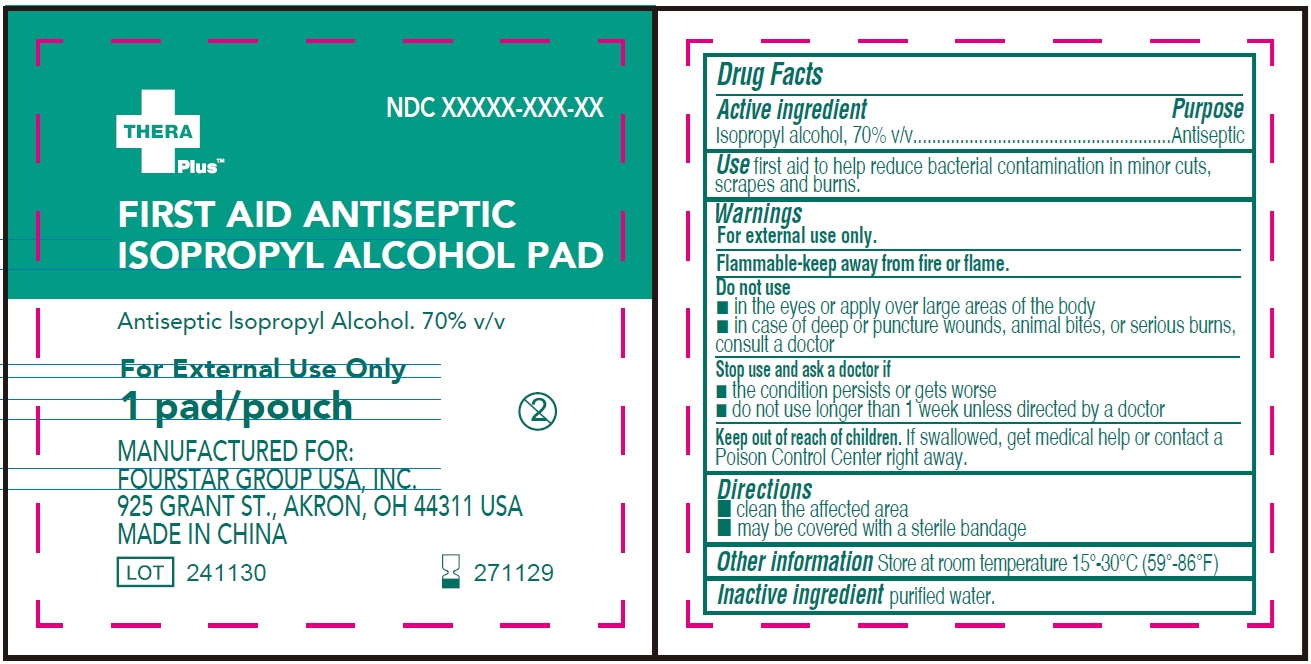 DRUG LABEL: First Aid Antiseptic Isopropyl Alcohol Pad
NDC: 80684-137 | Form: LIQUID
Manufacturer: Fourstar Group USA, Inc.
Category: otc | Type: HUMAN OTC DRUG LABEL
Date: 20241127

ACTIVE INGREDIENTS: ISOPROPYL ALCOHOL 70 mL/100 mL
INACTIVE INGREDIENTS: WATER

First Aid Antiseptic Isopropyl Alcohol Pad

Active ingredient

Isopropyl alcohol, 70% v/v

Purpose

Antiseptic

Use

first aid to help reduce bacterial contamination in minor cuts, scrapes and burns.

Warnings

For external use only.

Flammable -keep away from fire or flame.

Do not use

- in the eyes or apply over large areas of the body
- in case of deep or puncture wounds, animal bites, or serious burns, consult a doctor

Stop use and ask a doctor if

- the condition persists or gets worse
- do not use longer than 1 week unless directed by a doctor

Keep out of reach of children.

If swallowed, get medical help or contact a Poison Control Center right away.

Directions

- clean the affected area
- may be covered with a sterile bandage

Other information

Store at room temperature 15°-30°C (59°-86°F)

Inactive ingredient

purified water.